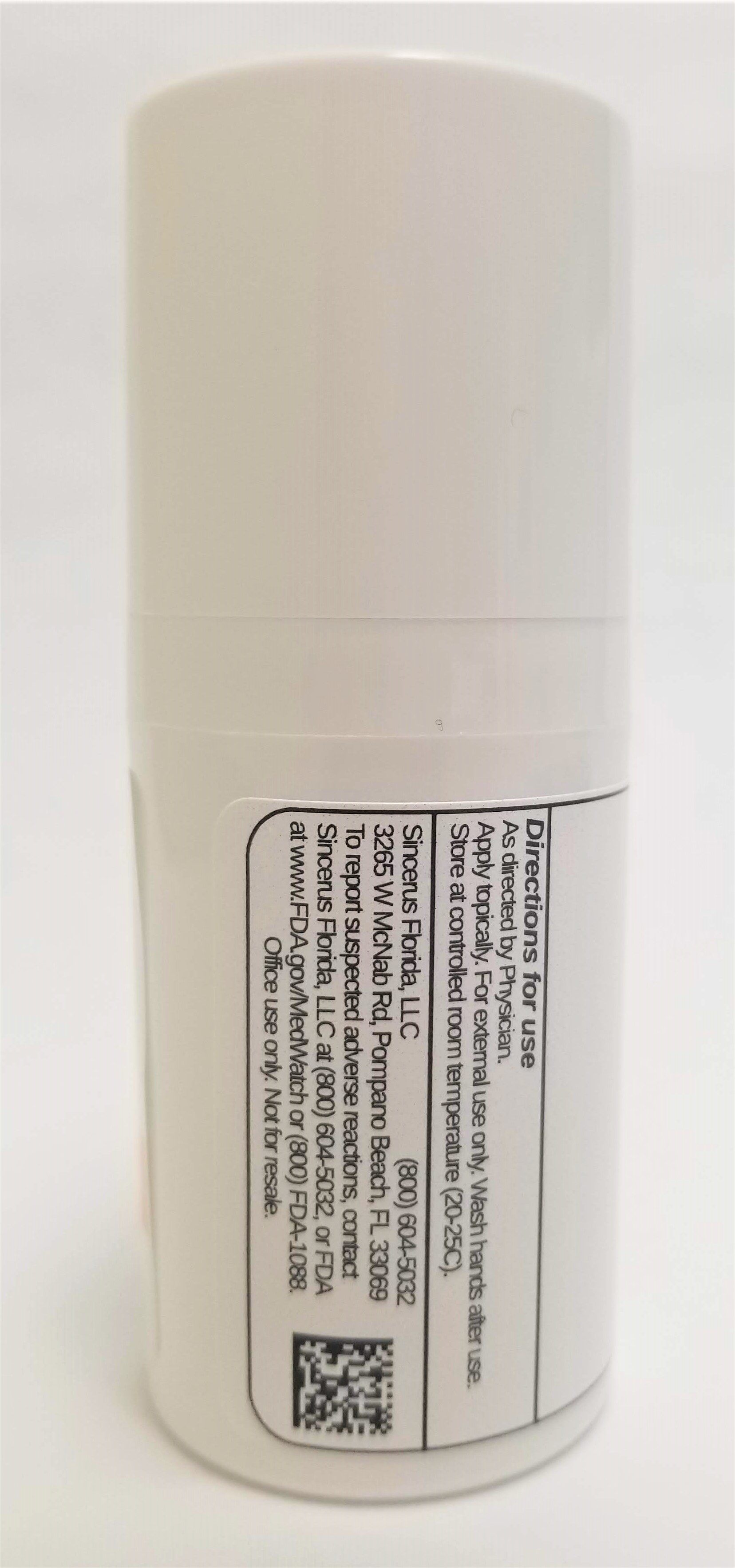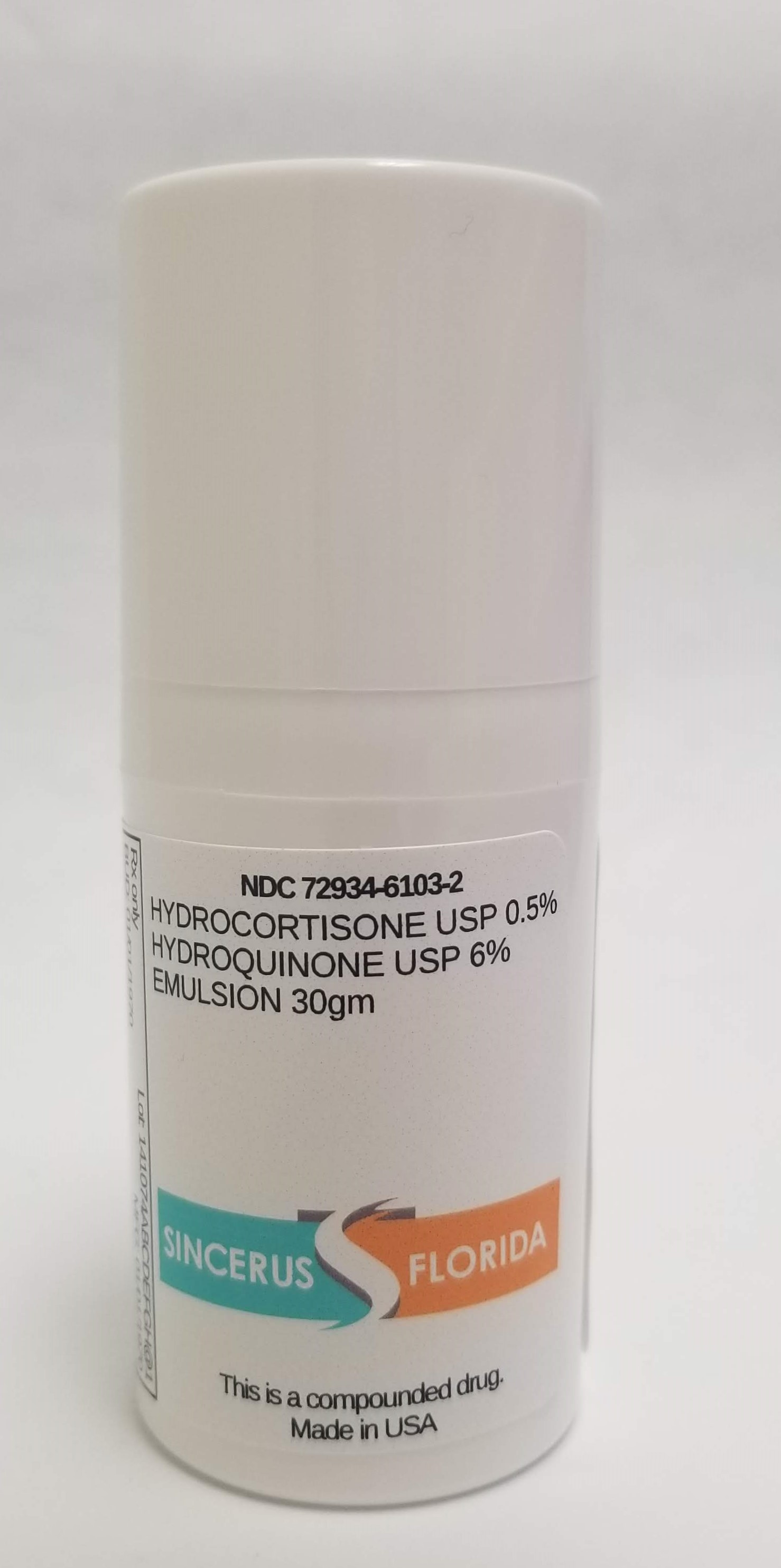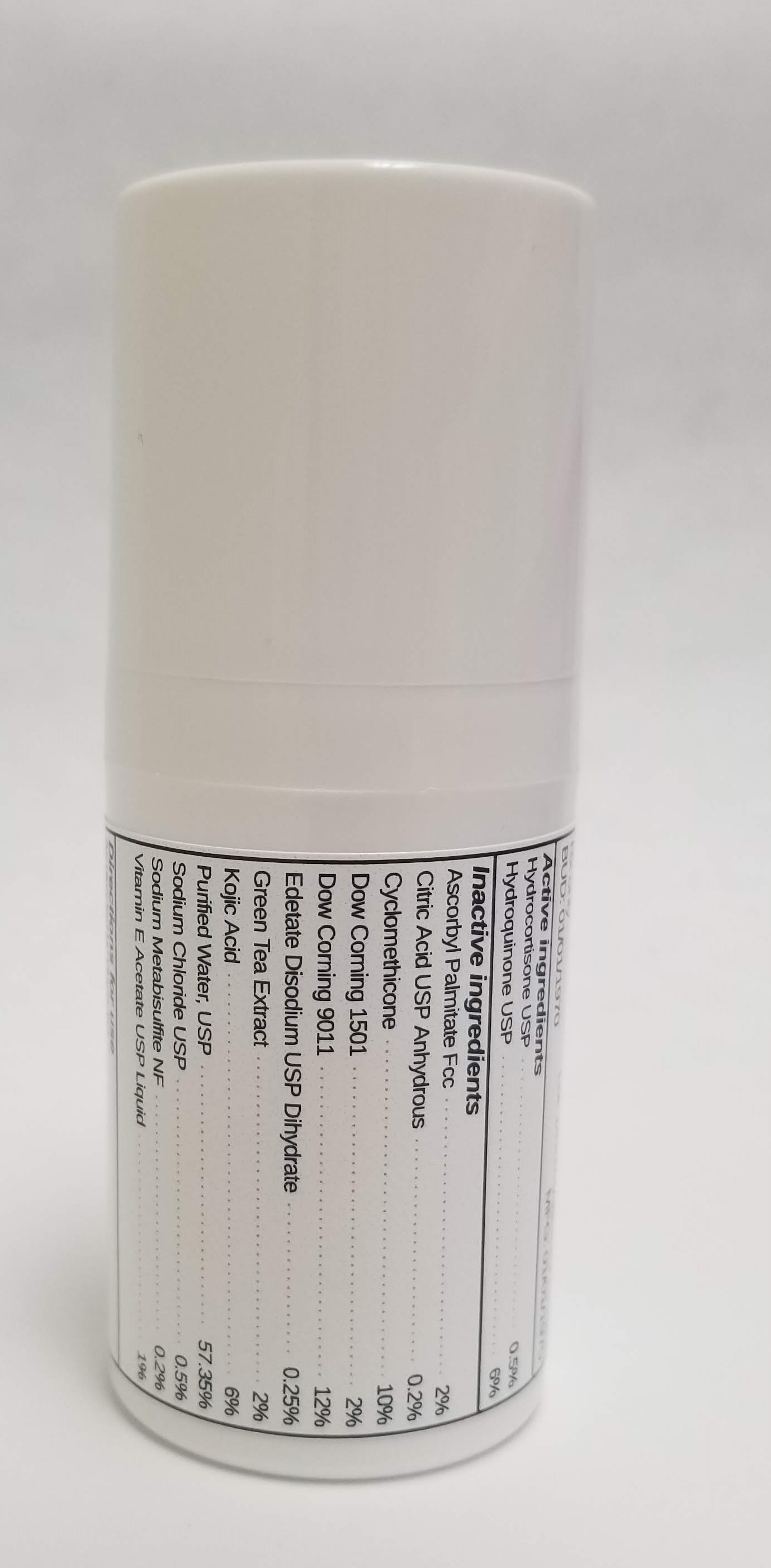 DRUG LABEL: HYDROCORTISONE 0.5% / HYDROQUINONE 6%
NDC: 72934-6103 | Form: EMULSION
Manufacturer: Sincerus Florida, LLC
Category: prescription | Type: HUMAN PRESCRIPTION DRUG LABEL
Date: 20190517

ACTIVE INGREDIENTS: HYDROCORTISONE 0.5 g/100 g; HYDROQUINONE 6 g/100 g

HYDROCORTISONE 0.5% / HYDROQUINONE 6%